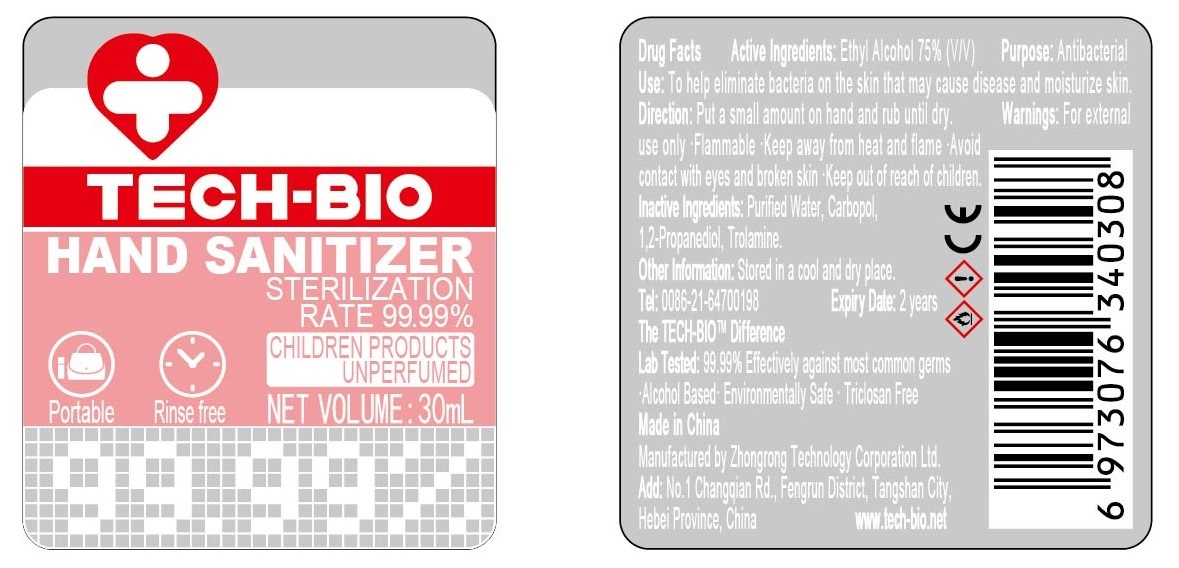 DRUG LABEL: Hand Sanitizer
NDC: 81191-003 | Form: GEL
Manufacturer: Zhongrong Technology Corporation Ltd.
Category: otc | Type: HUMAN OTC DRUG LABEL
Date: 20201214

ACTIVE INGREDIENTS: ALCOHOL 75 mL/100 mL
INACTIVE INGREDIENTS: TROLAMINE; CARBOMER HOMOPOLYMER, UNSPECIFIED TYPE; PROPYLENE GLYCOL 1,2-DISTEARATE; WATER

Hand sanitizer

Active Ingredient(s)

Ethyl Alcohol 75% v/v. Purpose: Antibacterial

Purpose

Antibacterial, Hand Sanitizer

Use

To help eliminate bacteria on the skin that may cause disease and moisturize skin.

Warnings

For external use only. Flammable. Keep away from heat and flame. Avoid contact with eyes and broken skin. Keep out of reach of children.

Do not use

- in children less than 2 months of age
- on open skin wounds

When using this product keep out of eyes, ears, and mouth. In case of contact with eyes, rinse eyes thoroughly with water.
Stop use and ask a doctor if irritation or rash occurs. These may be signs of a serious condition.
Keep out of reach of children. If swallowed, get medical help or contact a Poison Control Center right away.

Stop use and ask a doctor if irritation or rash occurs. These may be signs of a serious condition.

Keep out of reach of children. If swallowed, get medical help or contact a Poison Control Center right away.

Directions

- Place enough product on hands to cover all surfaces. Rub hands together until dry.
- Supervise children under 6 years of age when using this product to avoid swallowing.

Other information

- Store between 15-30C (59-86F)
- Avoid freezing and excessive heat above 40C (104F)

Inactive ingredients

purified water, Carbopol,Propylene Glycol, Trolamine.

Package Label - Principal Display Panel

30 mL NDC: 81191-003-01